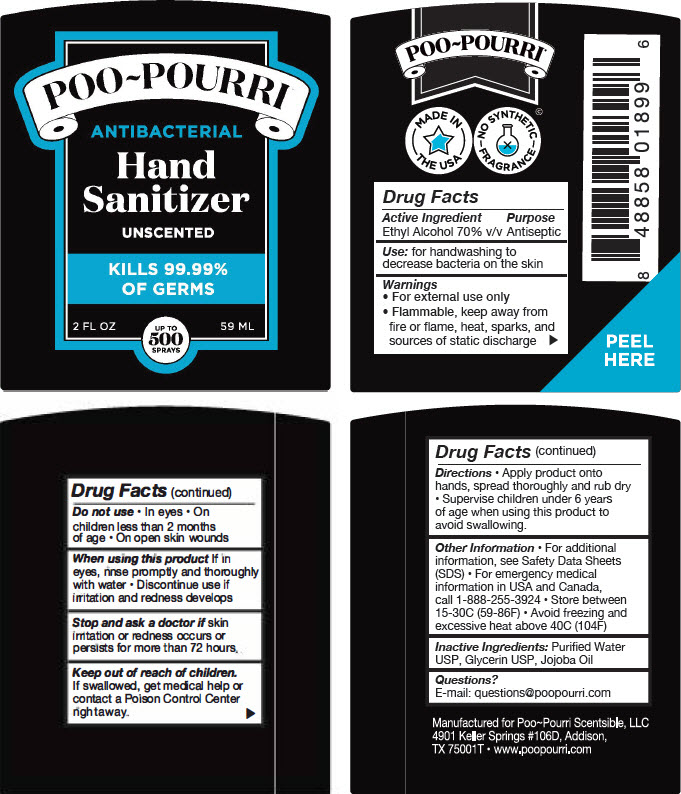 DRUG LABEL: Poo Pourri Antibacterial Hand Sanitizer - Unscented
NDC: 73754-102 | Form: LIQUID
Manufacturer: Scentsible, LLC
Category: otc | Type: HUMAN OTC DRUG LABEL
Date: 20200714

ACTIVE INGREDIENTS: ALCOHOL 70 mL/100 mL
INACTIVE INGREDIENTS: WATER; Glycerin; Jojoba Oil

Poo Pourri Antibacterial Hand Sanitizer - Unscented

Drug Facts

Active Ingredient

Ethyl Alcohol 70% v/v

Purpose

Antiseptic

Use

for handwashing to decrease bacteria on the skin

Warnings

- For external use only
- Flammable, keep away from fire or flame, heat, sparks, and sources of static discharge

Do not use

- Ineyes
- On children less than 2 months of age
- On open skin wounds

When using this product

If in eyes, rinse promptly and thoroughly with water

- Discontinue use if irritation and redness develops

STOP USE

Stop and ask a doctor if skin irritation or redness occurs or persists for more than 72 hours.

Keep out of reach of children. If swallowed, get medical help or contact a Poison Control Center rightaway.

Directions

- Apply product onto hands, spread thoroughly and rub dry
- Supervise children under 6 years of age when using this product to avoid swallowing.

Other Information

- For additional information, see Safety Data Sheets (SDS)
- For emergency medical information in USA and Canada, call 1-888-255-3924
- Store between 15-30C (59-86F)
- Avoid freezing and excessive heat above 40C (104F)

Inactive Ingredients

Purified Water USP, Glycerin USP, Jojoba Oil

Questions?

E-mail: questions@poopourri.com

PRINCIPAL DISPLAY PANEL - 59 ML Tube Label

POO~POURRI

ANTIBACTERIAL

Hand
Sanitizer

UNSCENTED

KILLS 99.99%
OF GERMS

2 FL OZ

UP TO
500
SPRAYS

59 ML